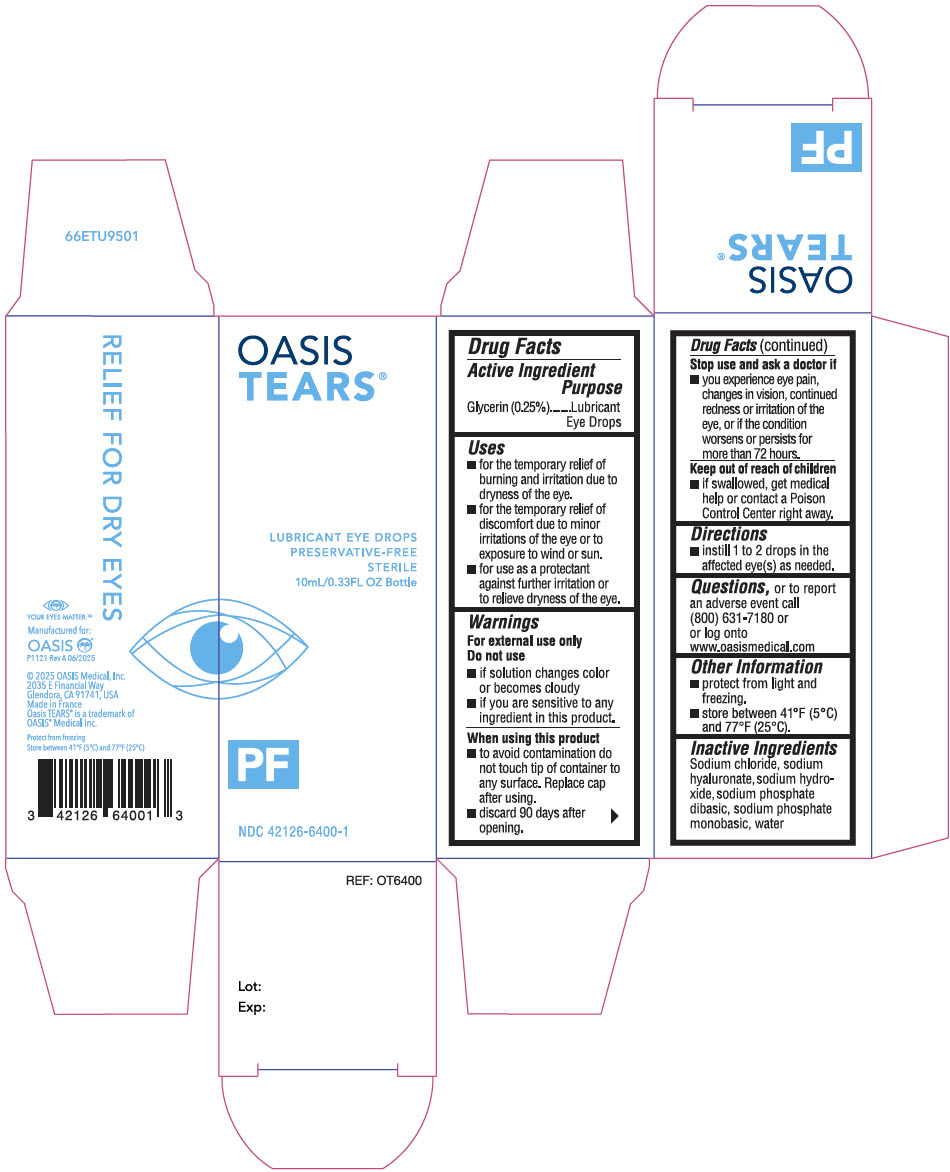 DRUG LABEL: Oasis Tears PF
NDC: 42126-6400 | Form: SOLUTION/ DROPS
Manufacturer: OASIS Medical, Inc.
Category: otc | Type: HUMAN OTC DRUG LABEL
Date: 20250912

ACTIVE INGREDIENTS: GLYCERIN 0.25 g/100 mL
INACTIVE INGREDIENTS: HYALURONATE SODIUM; SODIUM CHLORIDE; SODIUM PHOSPHATE, MONOBASIC, UNSPECIFIED FORM; SODIUM PHOSPHATE, DIBASIC, UNSPECIFIED FORM; SODIUM HYDROXIDE; WATER

Oasis Tears®
PF Preservative-Free Lubricant Eye Drops

Drug Facts

Active Ingredients

Glycerin (0.25%)

Purpose

lubricant Eye Drops

Uses

- For the temporary relief of burning and irritation due to dryness of the eye
- For the temporary relief of discomfort due to minor irritations of the eye or to exposure to wind or sun
- For use as a protectant against further irritation or to relieve dryness of the eye

Warnings

For external use only

Do not use

- If solution changes color or becomes cloudy
- If you are sensitive to any ingredient in this product

When using this product

- To avoid contamination do not touch tip of container to any surface
- Replace cap after using
- Discard 90 days after opening

Stop use and ask a doctor if

You experience eye pain, changes in vision, continued redness or irritation of the eye, or if the condition worsens or persists for more than 72 hours

Keep out of reach of children. If swallowed, get medical help or contact a Poison Control Center right away.

Directions

Instill 1 or 2 drops in the affected eye(s) as needed.

QUESTIONS

Questions, or to report an adverse event call (800) 631-7180 or or log onto www.oasismedical.com

Other Information

- protect from light and freezing.
- store between 41°F (5°C) and 77°F (25°C).

Inactive Ingredients

Sodium hyaluronate, sodium chloride, sodium hydroxide, sodium phosphate dibasic, sodium phosphate monobasic, water

PRINCIPAL DISPLAY PANEL - 10 mL Bottle Carton

OASIS
TEARS®

LUBRICANT EYE DROPS
PRESERVATIVE-FREE
STERILE
10mL/0.33FL OZ Bottle

PF

NDC 42126-6400-1